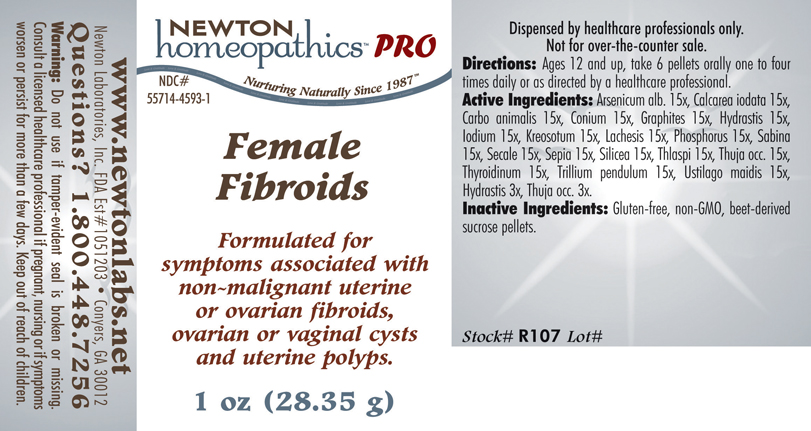 DRUG LABEL: Female Fibroids 
NDC: 55714-4593 | Form: PELLET
Manufacturer: Newton Laboratories, Inc.
Category: homeopathic | Type: HUMAN PRESCRIPTION DRUG LABEL
Date: 20110601

ACTIVE INGREDIENTS: Arsenic Trioxide 15 [hp_X]/1 g; Calcium Iodide 15 [hp_X]/1 g; Carbo Animalis 15 [hp_X]/1 g; Conium Maculatum Flowering Top 15 [hp_X]/1 g; Graphite 15 [hp_X]/1 g; Goldenseal 15 [hp_X]/1 g; Iodine 15 [hp_X]/1 g; Wood Creosote 15 [hp_X]/1 g; Lachesis Muta Venom 15 [hp_X]/1 g; Phosphorus 15 [hp_X]/1 g; Juniperus Sabina Leafy Twig 15 [hp_X]/1 g; Claviceps Purpurea Sclerotium 15 [hp_X]/1 g; Sepia Officinalis Juice 15 [hp_X]/1 g; Silicon Dioxide 15 [hp_X]/1 g; Capsella Bursa-pastoris 15 [hp_X]/1 g; Thuja Occidentalis Leafy Twig 15 [hp_X]/1 g; Thyroid, Unspecified 15 [hp_X]/1 g; Trillium Erectum Root 15 [hp_X]/1 g; Ustilago Maydis 15 [hp_X]/1 g
INACTIVE INGREDIENTS: Sucrose

Female Fibroids

INDICATIONS & USAGE SECTION

FEMALE FIBROIDS Formulated for symptoms associated with non-malignant uterine or ovarian fibroids, ovarian or vaginal cysts and uterine polyps.

DOSAGE & ADMINISTRATION SECTION

Directions: Ages 12 and up, take 6 pellets orally one to four times daily or as directed by a healthcare professional.

ACTIVE INGREDIENT SECTION

Arsenicum alb. 15x, Calcarea iodata 15x, Carbo animalis 15x, Conium 15x, Graphites 15x, Hydrastis 15x, Iodium 15x, Kreosotum 15x, Lachesis 15x, Phosphorus 15x, Sabina 15x, Secale 15x, Sepia 15x, Silicea 15x, Thlaspi 15x, Thuja occ. 15x, Thyroidinum 15x, Trillium pendulum 15x, Ustilago maidis 15x, Hydrastis 3x, Thuja occ. 3x.

PURPOSE SECTION

Formulated for symptoms associated with non-malignant uterine or ovarian fibroids, ovarian or vaginal cysts and uterine polyps.

INACTIVE INGREDIENT SECTION

Inactive Ingredients: Gluten-free, non-GMO, beet-derived sucrose pellets.

QUESTIONS? SECTION

www.newtonlabs.net Newton Laboratories, Inc. FDA Est # 1051203 - Conyers, GA 30012
Questions? 1.800.448.7256

WARNINGS SECTION

Warning: Do not use if tamper - evident seal is broken or missing. Consult a licensed healthcare professional if pregnant, nursing or if symptoms worsen or persist for more than a few days. Keep out of reach of children.

PREGNANCY OR BREAST FEEDING SECTION

Consult a licensed healthcare professional if pregnant or nursing or if symptoms worsen or persist for more than a few days.

KEEP OUT OF REACH OF CHILDREN SECTION

Keep out of reach of children.